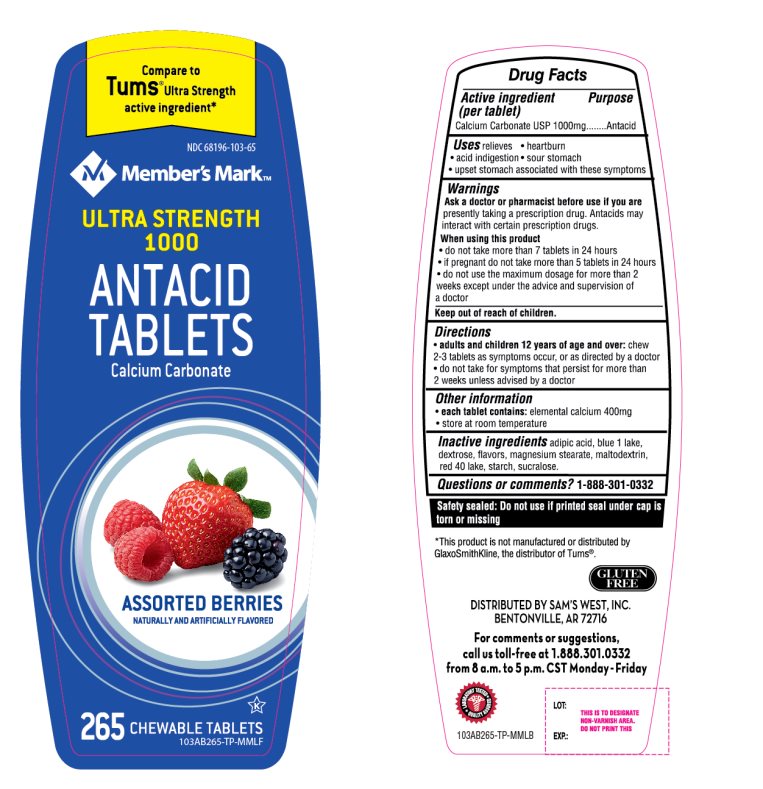 DRUG LABEL: Ultra Strength

NDC: 68196-103 | Form: TABLET, CHEWABLE
Manufacturer: SAM'S WEST INC
Category: otc | Type: HUMAN OTC DRUG LABEL
Date: 20251120

ACTIVE INGREDIENTS: CALCIUM CARBONATE 1000 mg/1 1
INACTIVE INGREDIENTS: ADIPIC ACID; FD&C BLUE NO. 1; DEXTROSE, UNSPECIFIED FORM; MAGNESIUM STEARATE; MALTODEXTRIN; FD&C RED NO. 40; STARCH, CORN; SUCRALOSE

Ultra Strength Antacid Calcium Carbonate Drug Facts

Active ingredient (per tablet)

Calcium Carbonate USP 1000mg

Purpose

Antacid

Uses

relieves

- heartburn
- acid indigestion
- sour stomach
- upset stomach associated with these symptoms

Ask a doctor or pharmacist before use if you are

presently taking a prescription drug. Antacids may interact with certain prescription drugs.

When using this product

- do not take more than 7 tablets in 24 hours
- if pregnant do not take more than 5 tablets in 24 hours
- do not use the maximum dosage for more than 2 weeks except under the advice and supervision of a doctor

Directions

- adults and children 12 years of age and over:chew 2-3 tablets as symptoms occur, or as directed by a doctor
- do not take for symptoms that persist for more than 2 weeks unless advised by a doctor

Other information

- each tablet contains: elemental calcium 400mg
- Store at room temperature

Inactive ingredients

adipic acid, blue 1 lake, dextrose, flavors, magnesium stearate, red 40 lake, starch, sucralose.

Questions or comments?

1-888-301-0332

Safety Sealed:

Do not use if printed seal under cap is torn or missing

Package/Label Principal Display Panel

Member’s Mark™

COMPARE TO TUMS®Ultra Strength active ingredient*

ULTRA STRENGTH 1000

ANTACID TABLETS

Calcium Carbonate

Assorted Berry Flavors

Naturally and Artificially Flavored

GLUTEN FREE

K PAREVE

DISTRIBUTED BY SAM’S WEST, INC.

BENTONVILLE, AR 72716

For comments or suggestions, call us toll-free at 1.888-301-0332 from 8 a.m. to 5 p.m. CST Monday-Friday

*This product is not manufactured or distributed by GlaxoSmithKline, the distributor of Tums®.

Package Label 265 Chewable Tablets